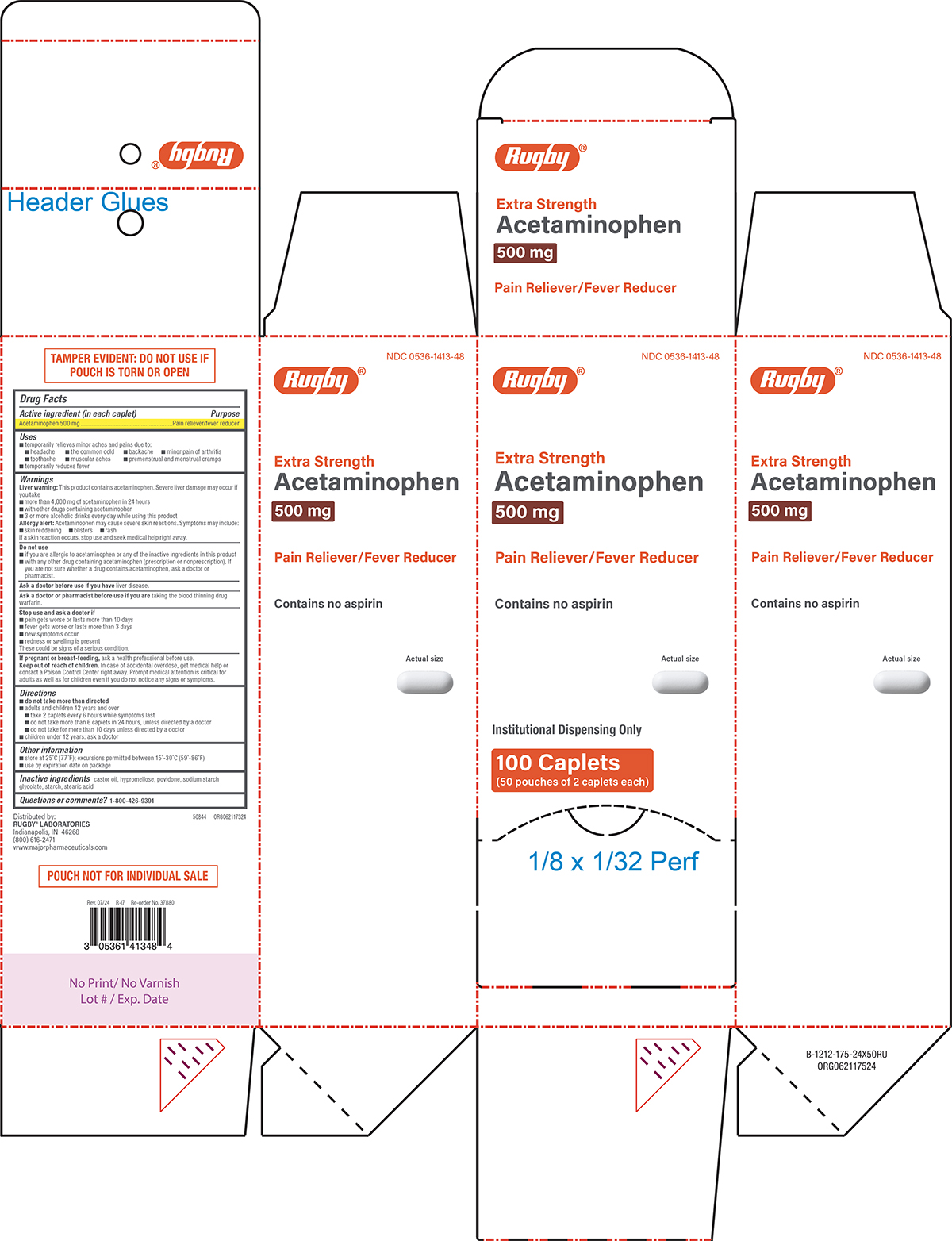 DRUG LABEL: Acetaminophen
NDC: 0536-1413 | Form: TABLET, FILM COATED
Manufacturer: Rugby Laboratories
Category: otc | Type: HUMAN OTC DRUG LABEL
Date: 20251022

ACTIVE INGREDIENTS: ACETAMINOPHEN 500 mg/1 1
INACTIVE INGREDIENTS: CASTOR OIL; HYPROMELLOSE, UNSPECIFIED; POVIDONE, UNSPECIFIED; SODIUM STARCH GLYCOLATE TYPE A POTATO; STARCH, CORN; STEARIC ACID

Pain Reliever

Active ingredient (in each caplet)

Acetaminophen 500 mg

Purpose

Pain reliever/fever reducer

Uses

- temporarily relieves minor aches and pains due to:
  - headache
  - the common cold
  - backache
  - minor pain of arthritis
  - toothache
  - muscular aches
  - premenstrual and menstrual cramps
- temporarily reduces fever

Warnings

Liver warning: This product contains acetaminophen. Severe liver damage may occur if you take

- more than 4,000 mg of acetaminophen in 24 hours
- with other drugs containing acetaminophen
- 3 or more alcoholic drinks every day while using this product

Allergy alert: Acetaminophen may cause severe skin reactions. Symptoms may include:

- skin reddening
- blisters
- rash

If a skin reaction occurs, stop use and seek medical help right away.

Do not use

- if you are allergic to acetaminophen or any of the inactive ingredients in this product
- with any other drug containing acetaminophen (prescription or nonprescription). If you are not sure whether a drug contains acetaminophen, ask a doctor or pharmacist.

Ask a doctor before use if you have

liver disease.

Ask a doctor or pharmacist before use if you are

taking the blood thinning drug warfarin.

Stop use and ask a doctor if

- pain gets worse or lasts more than 10 days
- fever gets worse or lasts more than 3 days
- new symptoms occur
- redness or swelling is present

These could be signs of a serious condition.

If pregnant or breast-feeding,

ask a health professional before use.

Keep out of reach of children.

In case of accidental overdose, get medical help or contact a Poison Control Center right away. Prompt medical attention is critical for adults as well as for children even if you do not notice any signs or symptoms.

Directions

- do not take more than directed
- adults and children 12 years and over
  - take 2 caplets every 6 hours while symptoms last
  - do not take more than 6 caplets in 24 hours, unless directed by a doctor
  - do not take for more than 10 days unless directed by a doctor
- children under 12 years: ask a doctor

Other information

- store at 25°C (77°F); excursions permitted between 15°-30°C (59°-86°F)
- use by expiration date on package

Inactive ingredients

castor oil, hypromellose, povidone, sodium starch glycolate, starch, stearic acid

Questions or comments?

1-800-426-9391

Principal Display Panel

Rugby®

NDC 0536-1413-48

Extra Strength
Acetaminophen
500 mg

Pain Reliever/Fever Reducer

Contains no aspirin

Actual size

Institutional Dispensing Only

100 Caplets
(50 pouches of 2 caplets each)

TAMPER EVIDENT: DO NOT USE IF
POUCH IS TORN OR OPEN

POUCH NOT FOR INDIVIDUAL SALE

Distributed by:
RUGBY® LABORATORIES
Indianapolis, IN 46268
(800) 616-2471
www.majorpharmaceuticals.com

50844 ORG062117524

Rugby 44-175 Institutional Dispensing